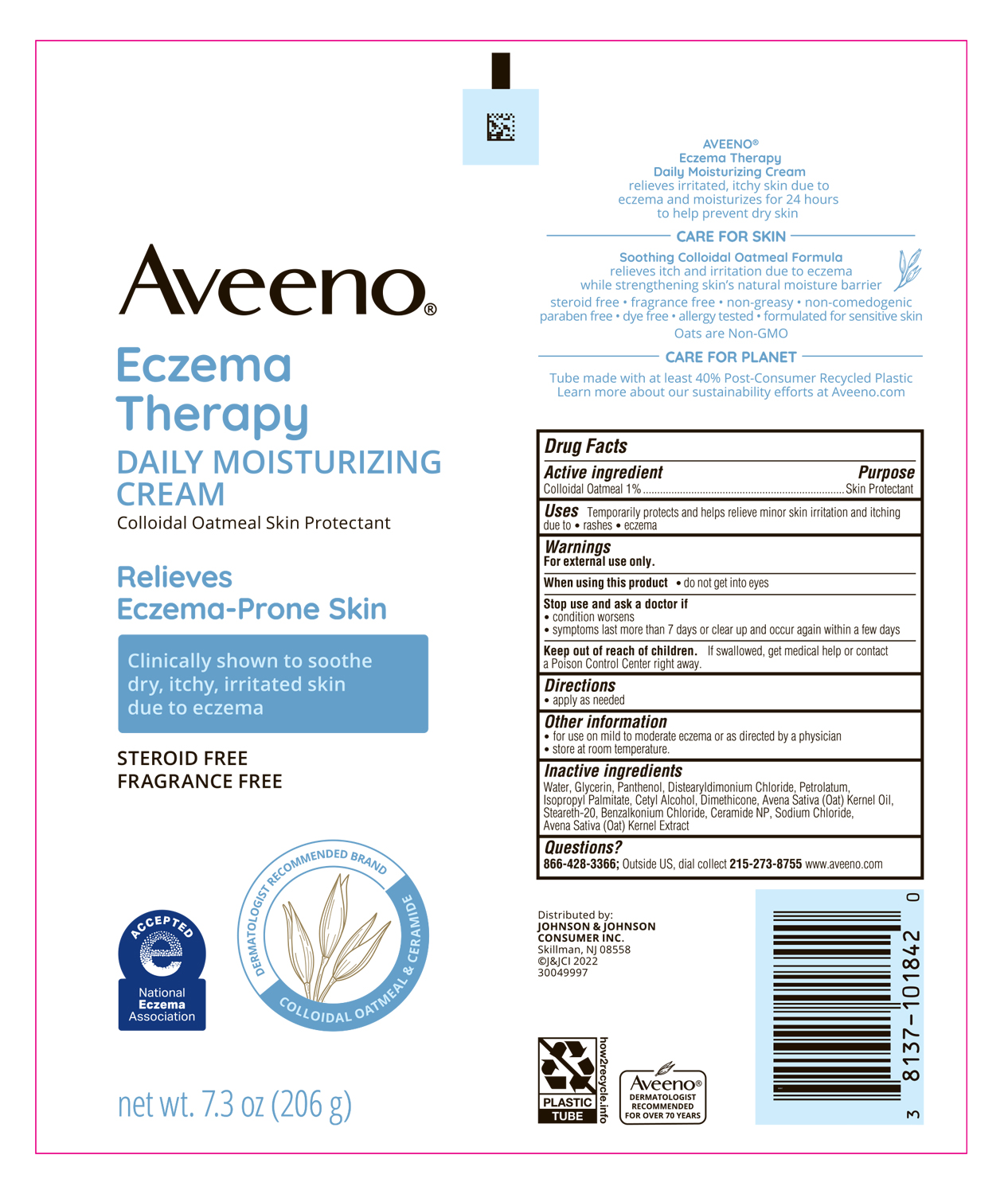 DRUG LABEL: Aveeno Eczema Therapy daily moisturizing
NDC: 69968-0421 | Form: CREAM
Manufacturer: Kenvue Brands LLC
Category: otc | Type: HUMAN OTC DRUG LABEL
Date: 20241105

ACTIVE INGREDIENTS: OATMEAL 10 mg/1 g
INACTIVE INGREDIENTS: WATER; GLYCERIN; PANTHENOL; DISTEARYLDIMONIUM CHLORIDE; PETROLATUM; ISOPROPYL PALMITATE; CETYL ALCOHOL; DIMETHICONE; OAT KERNEL OIL; STEARETH-20; BENZALKONIUM CHLORIDE; CERAMIDE NP; SODIUM CHLORIDE; OAT

Aveeno® Eczema Therapy Daily Moisturizing Cream

Drug Facts

Active ingredient

Colloidal oatmeal 1%

Purpose

Skin protectant

Uses

Temporarily protects and helps relieve minor skin irritation and itching due to:

- rashes
- eczema

Warnings

For external use only. When using this product

- do not get into eyes.

Stop use and ask a doctor if

- condition worsens
- symptoms last more than 7 days or clear up and occur again within a few days.

Keep out of reach of children. If swallowed, get medical help or contact a Poison Control Center right away.

Directions

apply as needed

Other information

- for use on mild to moderate eczema or as directed by a physician.
- store at room temperature.

Inactive ingredients

Water, Glycerin, Panthenol, Distearyldimonium Chloride, Petrolatum, Isopropyl Palmitate, Cetyl Alcohol, Dimethicone, Avena Sativa (Oat) Kernel Oil, Steareth-20, Benzalkonium Chloride, Ceramide NP, Sodium Chloride, Avena Sativa (Oat) Kernel Extract

Questions?

866-428-3366; Outside US, dial collect 215-273-8755 www.aveeno.com

Distributed by:
JOHNSON & JOHNSON
CONSUMER INC.
Skillman, NJ 08558

PRINCIPAL DISPLAY PANEL - 206 g Tube Label

Aveeno®

Eczema

Therapy

DAILY MOISTURIZING

CREAM

Colloidal Oatmeal Skin Protectant

Relieves

Eczema-prone skin

Clinically shown to soothe

dry, itchy, irritated skin

due to eczema

STEROID FREE

FRAGRANCE FREE

DERMATOLOGIST RECOMMENDED BRAND

COLLOIDAL OATMEAL & CERAMIDE

ACCEPTED

e

NATIONAL

ECZEMA

ASSOCIATION

net wt. 7.3 oz (206 g)